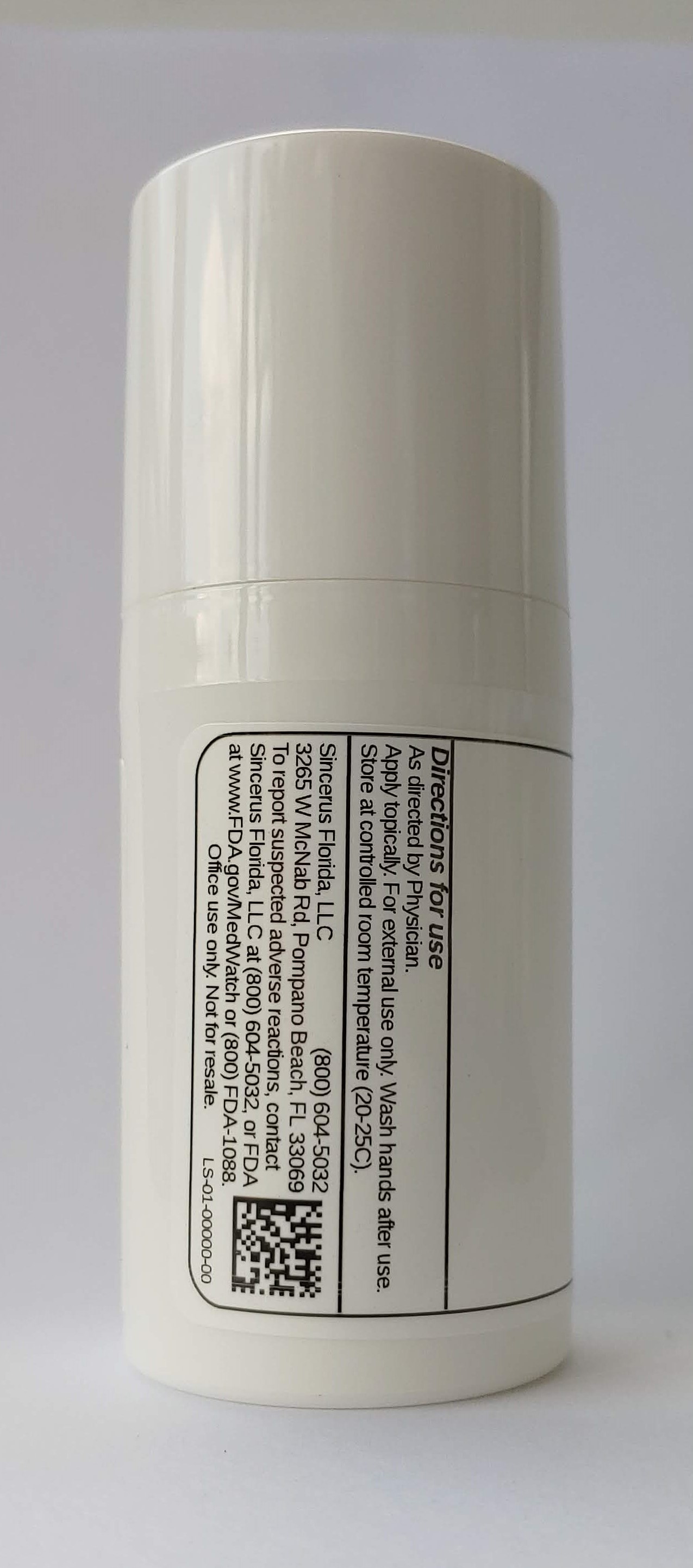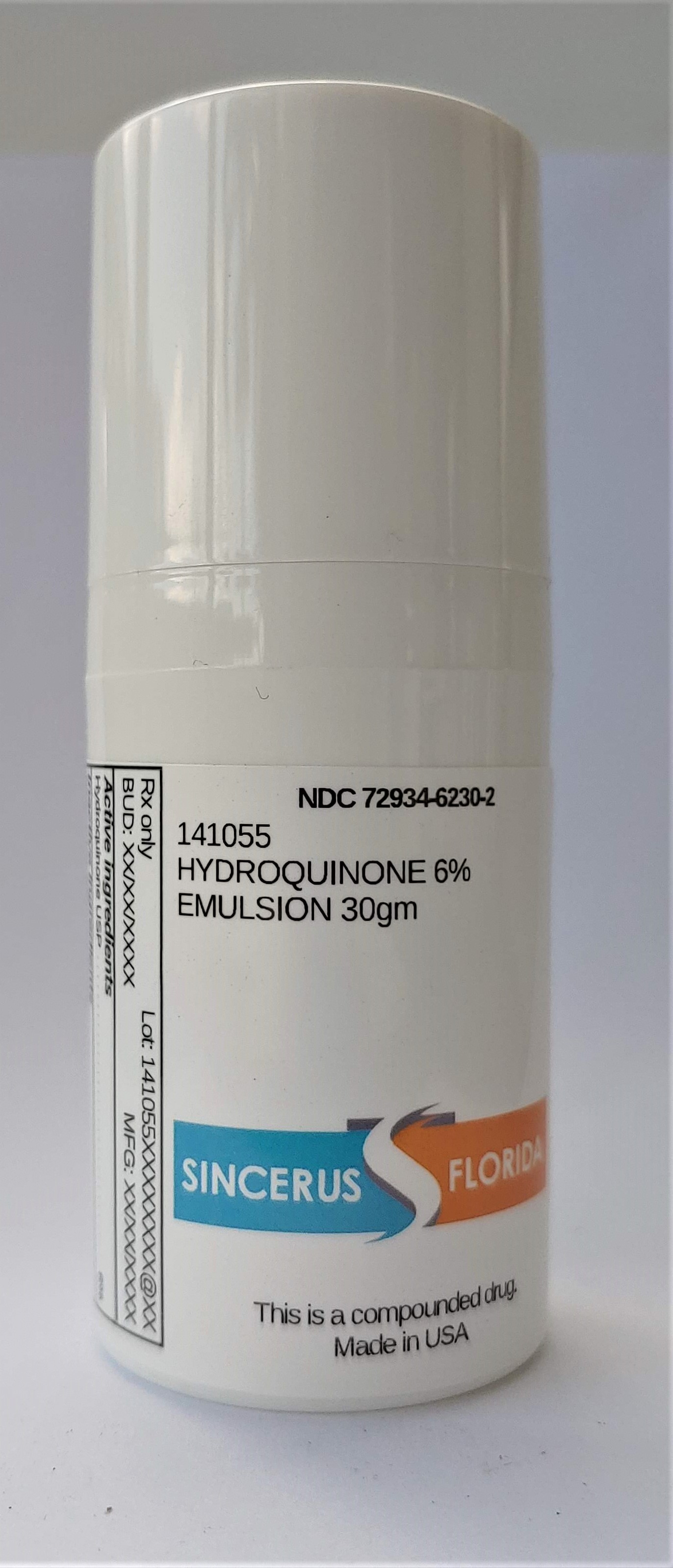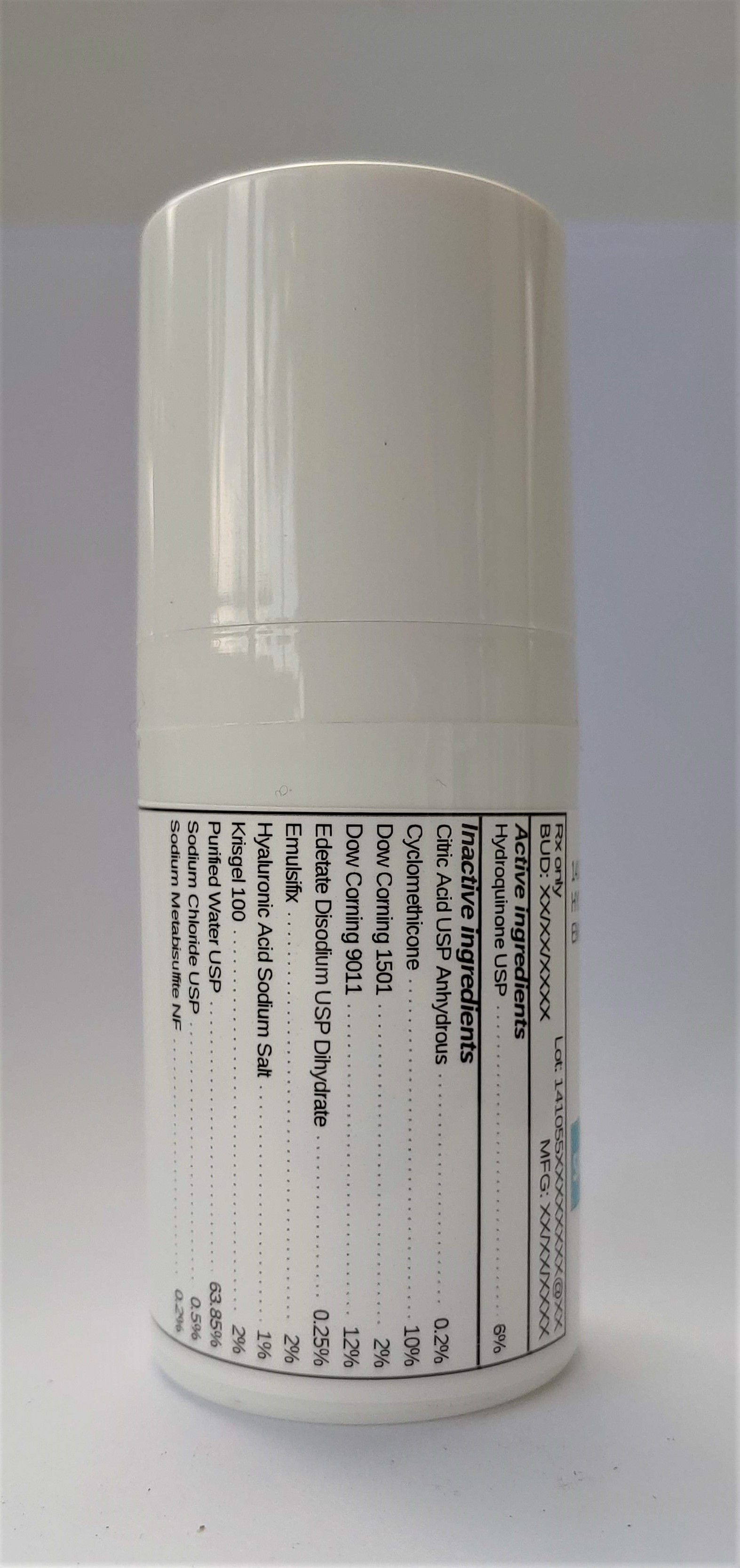 DRUG LABEL: 141055 HYDROQUINONE 6%
NDC: 72934-6230 | Form: EMULSION
Manufacturer: Sincerus Florida, LLC
Category: prescription | Type: HUMAN PRESCRIPTION DRUG LABEL
Date: 20200702

ACTIVE INGREDIENTS: HYDROQUINONE 6 g/100 g

141055 HYDROQUINONE 6%